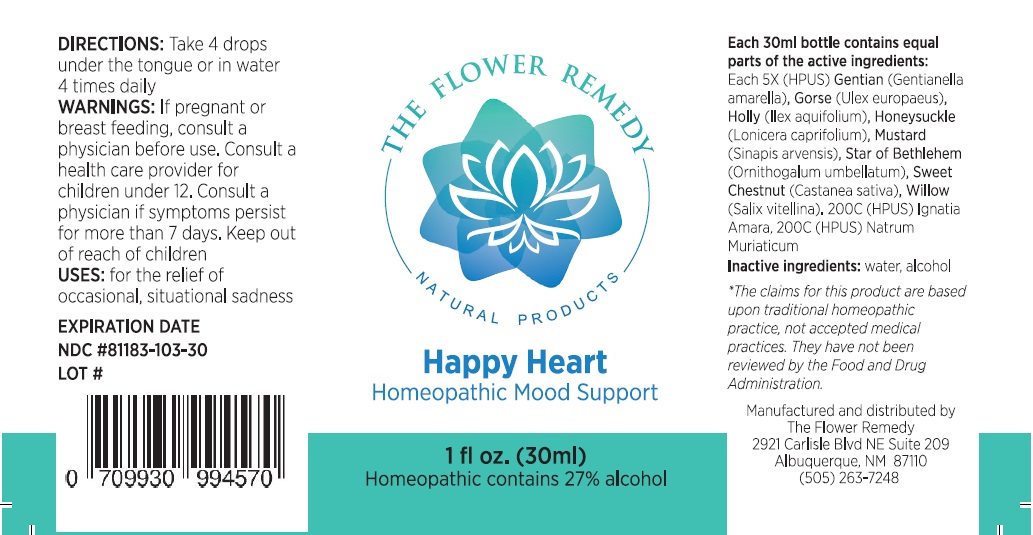 DRUG LABEL: THE FLOWER REMEDY Happy Heart
NDC: 81183-103 | Form: LIQUID
Manufacturer: The Flower Remedy
Category: homeopathic | Type: HUMAN OTC DRUG LABEL
Date: 20251203

ACTIVE INGREDIENTS: GENTIANELLA AMARELLA FLOWER 5 [hp_X]/30 mL; ULEX EUROPAEUS FLOWER 5 [hp_X]/30 mL; ILEX AQUIFOLIUM FLOWERING TOP 5 [hp_X]/30 mL; LONICERA CAPRIFOLIUM FLOWERING TOP 5 [hp_X]/30 mL; RHAMPHOSPERMUM ARVENSE FLOWERING/FRUITING TOP 5 [hp_X]/30 mL; ORNITHOGALUM UMBELLATUM FLOWERING TOP 5 [hp_X]/30 mL; CASTANEA SATIVA FLOWER 5 [hp_X]/30 mL; SALIX ALBA FLOWERING TOP 5 [hp_X]/30 mL; STRYCHNOS IGNATII SEED 200 [hp_C]/30 mL; SODIUM CHLORIDE 200 [hp_C]/30 mL
INACTIVE INGREDIENTS: WATER; ALCOHOL

THE FLOWER REMEDY NATURAL PRODUCTS Happy Heart

Active Ingredients:

Each 30 ml bottle contains equal parts of the active ingredients:
Each 5X (HPUS) Gentian (Gentianella amarella), Gorse (Ulex europaeus), Holly (Ilex aquifolium), Honeysuckle (Lonicera caprifolium), Mustard (Sinapis arvensis), Star of Bethlehem (Ornithogalum umbellatum), Sweet Chestnut (Castanea sativa), Willow (Salix vitellina). 200C (HPUS) Ignatia Amara, 200C (HPUS) Natrum Muriaticum

Purpose:

Mood Support

USES:

for the relief of occasional, situational sadness

DIRECTIONS:

Take 4 drops under the tongue or in water 4 times daily.

WARNINGS:

If pregnant or breast feeding, consult a physician before use. Consult a health care provider for children under 12. Consult a physician if symptoms persist for more than 7 days.

Keep out of reach of children.

Inactive ingredients:

water, alcohol

THE FLOWER REMEDY
NATURAL PRODUCTS

Homeopathic Mood Support

Homeopathic contains 27% alcohol

*The claims for this product are based upon traditional homeopathic practice, not accepted medical practices. They have not been reviewed by the Food and Drug Administration.

Manufactured and distributed by
The Flower Remedy
2921 Carlisle Blvd NE Suite 209
Albuquerque, NM 87110
(505) 263-7248